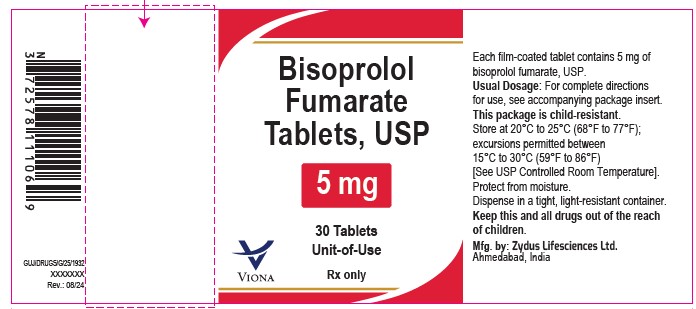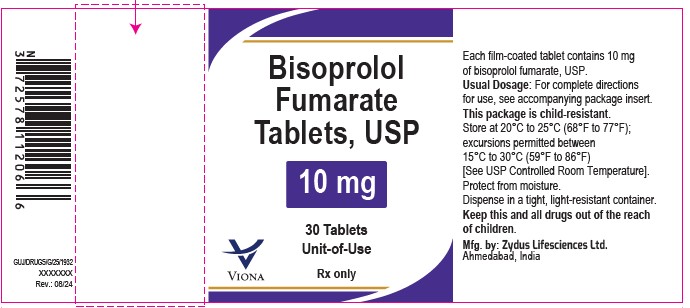 DRUG LABEL: Bisoprolol Fumarate
NDC: 70771-1726 | Form: TABLET, FILM COATED
Manufacturer: Zydus Lifesciences Limited
Category: prescription | Type: HUMAN PRESCRIPTION DRUG LABEL
Date: 20240814

ACTIVE INGREDIENTS: BISOPROLOL FUMARATE 5 mg/1 1
INACTIVE INGREDIENTS: ALUMINUM OXIDE; ANHYDROUS DIBASIC CALCIUM PHOSPHATE; BUTYLATED HYDROXYANISOLE; CROSPOVIDONE (12 MPA.S AT 5%); D&C YELLOW NO. 10 ALUMINUM LAKE; FD&C RED NO. 40; HYPROMELLOSE 2910 (6 MPA.S); MAGNESIUM STEARATE; MICROCRYSTALLINE CELLULOSE; POLYETHYLENE GLYCOL 6000; SILICON DIOXIDE; TITANIUM DIOXIDE

Bisoprolol Fumarate Tablets, USP

PACKAGE LABEL.PRINCIPAL DISPLAY PANEL

NDC 70771-1726-3

Bisoprolol Fumarate Tablets USP, 5 mg

30 Tablets

Unit-of-Use

Rx only

NDC 70771-1727-3

Bisoprolol Fumarate Tablets USP, 10 mg

30 Tablets

Unit-of-Use

Rx only